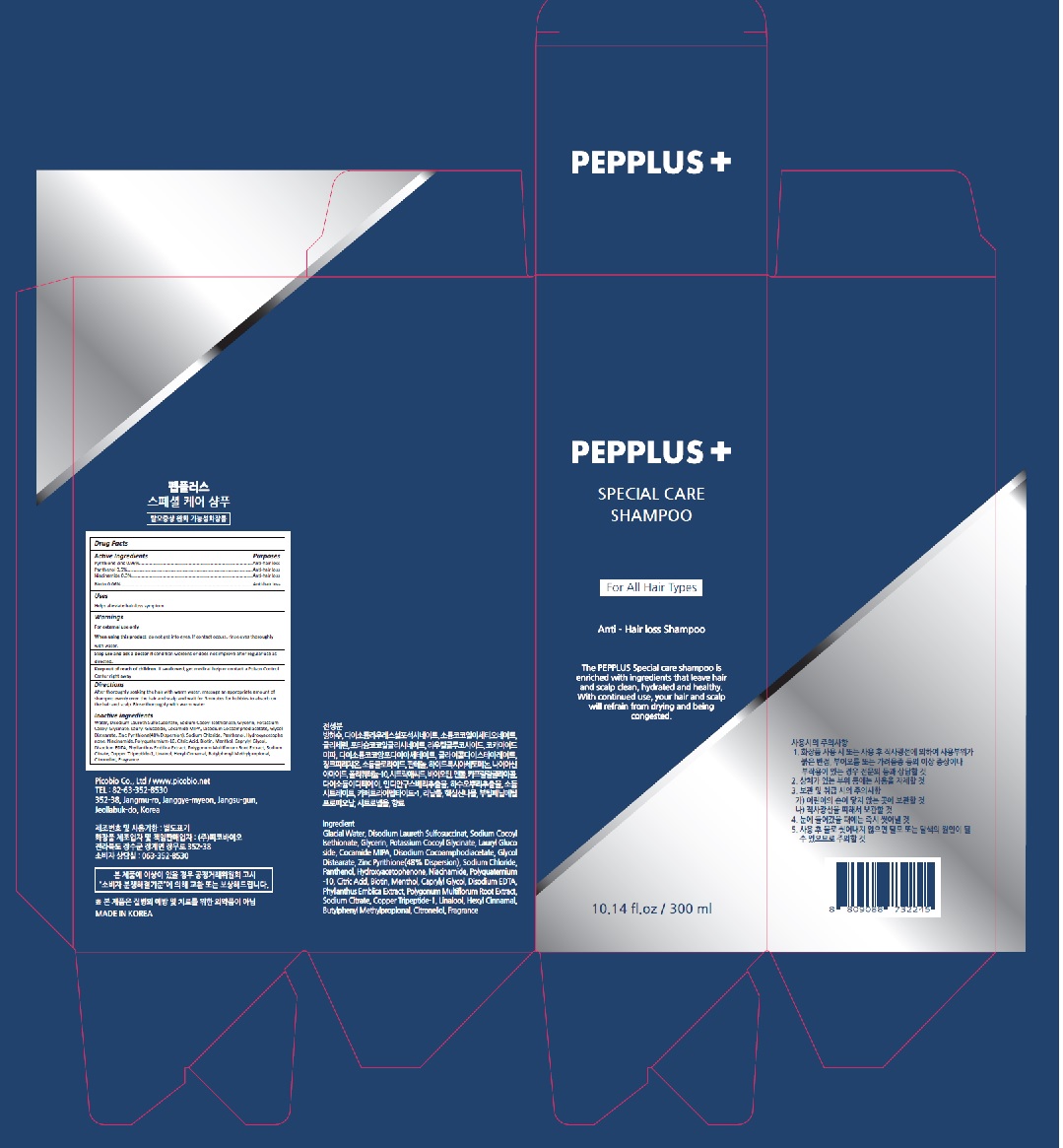 DRUG LABEL: PEPPLUS SPECIAL CARE
NDC: 72211-009 | Form: SHAMPOO
Manufacturer: Picobio Co., Ltd
Category: otc | Type: HUMAN OTC DRUG LABEL
Date: 20211029

ACTIVE INGREDIENTS: PYRITHIONE ZINC 2.88 mg/300 mL; PANTHENOL 1.5 mg/300 mL; NIACINAMIDE 0.9 mg/300 mL; BIOTIN 0.18 mg/300 mL
INACTIVE INGREDIENTS: WATER; DISODIUM LAURETH SULFOSUCCINATE; SODIUM COCOYL ISETHIONATE; GLYCERIN; POTASSIUM COCOYL GLYCINATE; LAURYL GLUCOSIDE; COCO MONOISOPROPANOLAMIDE; DISODIUM COCOAMPHODIACETATE; GLYCOL DISTEARATE; SODIUM CHLORIDE; HYDROXYACETOPHENONE; POLYQUATERNIUM-10 (1000 MPA.S AT 2%); CITRIC ACID MONOHYDRATE; MENTHOL, UNSPECIFIED FORM; CAPRYLYL GLYCOL; EDETATE DISODIUM ANHYDROUS

72211-009_V1

ACTIVE INGREDIENT

Pyrithione Zinc 0.96%
Panthenol 0.5%
Niacinamide 0.3%
Biotin 0.06%

PURPOSE

Anti-hair loss

INDICATIONS AND USAGE

Helps alleviate hair-loss symptom

DOSAGE AND ADMINISTRATION

After thoroughly soaking the hair with warm water, massage an appropriate amount of shampoo evenly over the hair and scalp and wait for 3minutes for bubbles to absorb on the hair and scalp. Rinse thoroughly with warm water.

WARNINGS

For external use only.
When using this product, do not get into eyes. If contact occurs, rinse eyes thoroughly with water.

Stop use and ask a doctor if condition worsens or does not improve after regular use as directed.

KEEP OUT OF REACH OF CHILDREN

Keep out of reach of the children. If product is swallowed, get medical help or contact a poison control center right away.

INACTIVE INGREDIENT

Water, Disodium Laureth Sulfosuccinate, Sodium Cocoyl Isethionate, Glycerin, Potassium Cocoyl Glycinate, Lauryl Glucoside, Cocamide MIPA, Disodium Cocoamphodiacetate, Glycol Distearate, Sodium Chloride, Hydroxyacetophenone, Polyquaternium-10, Citric Acid, Menthol, Caprylyl Glycol, Disodium EDTA, Phyllanthus Emblica Extract, Polygonum Multiflorum Root Extract, Sodium Citrate, Copper Tripeptide-1, Linalool, Hexyl Cinnamal, Butylphenyl Methylpropional, Citronellol, Fragrance